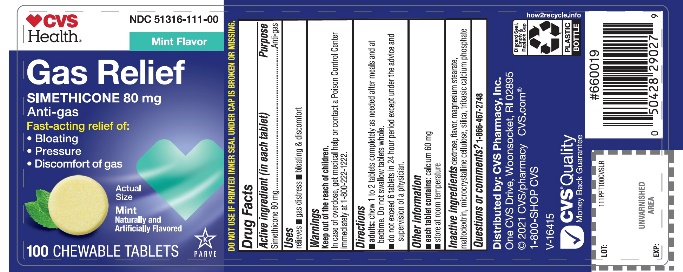 DRUG LABEL: CVS PHARMACY

NDC: 51316-111 | Form: TABLET, CHEWABLE
Manufacturer: CVS
Category: otc | Type: HUMAN OTC DRUG LABEL
Date: 20251208

ACTIVE INGREDIENTS: DIMETHICONE, UNSPECIFIED 80 mg/1 1
INACTIVE INGREDIENTS: DEXTROSE, UNSPECIFIED FORM; MAGNESIUM STEARATE; MALTODEXTRIN; MICROCRYSTALLINE CELLULOSE; SILICON DIOXIDE; TRICALCIUM PHOSPHATE

CVS Simethicone Gas Relief 100 Chewable Tablets

Active ingredient (in each tablet)

Simethicone 80 mg

Purpose

Antigas

Uses

relieves:

- bloating & discomfort
- gas distress

Directions

- adults: chew 1 to 2 tablets completely as needed after meals and at bedtime. Do not swallow tablets whole
- do not exceed 6 tablets in 24 hours period except under the advice and supervision of a physician.

Other information

- each tablet contains:calcium 60 mg
- store at room temperature

Inactive ingredients

dextrose, flavor, magnesium stearate, maltodextrin, microcrystalline cellulose, silica, tribasic calcium phosphate

Questions or comments?

1-866-467-2748

Principal Display Panel

NDC 51316-111-00

Gas Relief

Simethicone 80 mg / Antigas

For Fast Relief of Gas Distress Bloating & Discomfort

Mint Flavor

Naturally and Artificially Flavored

100 CHEWABLE TABLETS

Distributed by